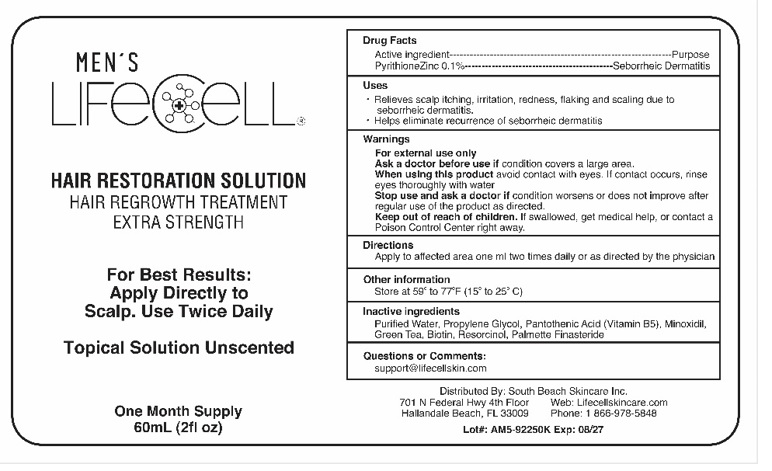 DRUG LABEL: LIFECELL Mens
NDC: 82627-004 | Form: LIQUID
Manufacturer: AmWiner & Raphe Holdings LLC
Category: otc | Type: HUMAN OTC DRUG LABEL
Date: 20221102

ACTIVE INGREDIENTS: PYRITHIONE ZINC 0.1 g/100 mL
INACTIVE INGREDIENTS: WATER; PROPYLENE GLYCOL; PANTHENOL; MINOXIDIL; GREEN TEA LEAF; BIOTIN; FINASTERIDE; SAW PALMETTO

Active Ingredient

Pyrithione Zinc 0.1%

Purpose

Seborrheic dermatitis

Uses

•Relieves scalp itching, irritation, redness, flaking and scaling due to seborrheic dermatitis.
• Helps eliminate recurrence of seborrheic dermatitis

Warnings

For external use only
Ask a doctor before use if condition covers a large area.
When using this product avoid contact with eyes. If contact occurs, rinse eyes thoroughly with water
Stop use and ask a doctor if condition worsens or does not improve after regular use of the product as directed.
Keep out of reach of children. If swallowed, get medical help, or contact a Poison Control Center right away.

Directions

Apply to affected area one ml two times daily or as directed by the physician

Other information

• Store at 59° to 77°F (15° to 25°C)

Inactive ingredients

Purified Water, Propylene Glycol, Vitamin B5, Minoxidil, Green Tea, Biotin, Saw Palmetto, Finasteride.

Questions or Comments

Support@lifecellskin.com